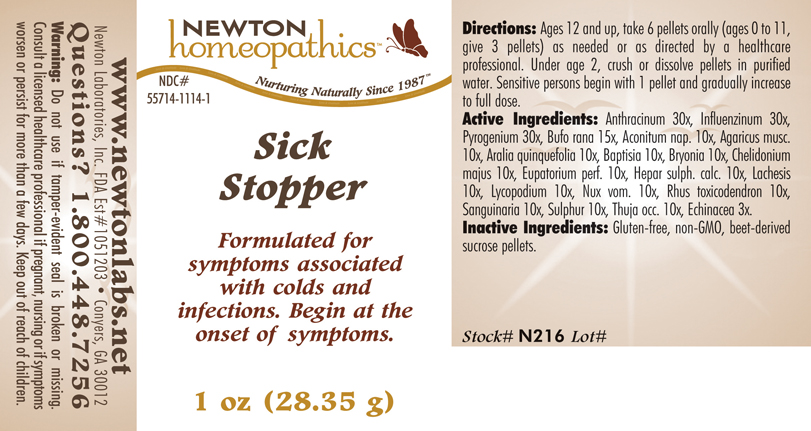 DRUG LABEL: Sick Stopper 
NDC: 55714-1114 | Form: PELLET
Manufacturer: Newton Laboratories, Inc.
Category: homeopathic | Type: HUMAN OTC DRUG LABEL
Date: 20110301

ACTIVE INGREDIENTS: Bacillus Anthracis Immunoserum Rabbit 30 [hp_X]/1 g; Influenza A Virus 30 [hp_X]/1 g; Rancid Beef 30 [hp_X]/1 g; Bufo Bufo Cutaneous Gland 15 [hp_X]/1 g; Aconitum Napellus 10 [hp_X]/1 g; Amanita Muscaria Var. Muscaria Fruiting Body 10 [hp_X]/1 g; American Ginseng 10 [hp_X]/1 g; Baptisia Tinctoria 10 [hp_X]/1 g; Bryonia Alba Root 10 [hp_X]/1 g; Chelidonium Majus 10 [hp_X]/1 g; Eupatorium Perfoliatum Flowering Top 10 [hp_X]/1 g; Calcium Sulfide 10 [hp_X]/1 g; Lachesis Muta Venom 10 [hp_X]/1 g; Lycopodium Clavatum Spore 10 [hp_X]/1 g; Strychnos Nux-vomica Seed 10 [hp_X]/1 g; Toxicodendron Pubescens Leaf 10 [hp_X]/1 g; Sanguinaria Canadensis Root 10 [hp_X]/1 g; Sulfur 10 [hp_X]/1 g; Thuja Occidentalis Leafy Twig 10 [hp_X]/1 g; Echinacea, Unspecified 3 [hp_X]/1 g; Influenza B Virus 30 [hp_X]/1 g
INACTIVE INGREDIENTS: Sucrose

Sick Stopper

INDICATIONS & USAGE SECTION

Sick Stopper Formulated for symptoms associated with colds and infections. Begin at the onset of symptoms.

DOSAGE & ADMINISTRATION SECTION

Directions: Ages 12 and up, take 6 pellets orally (ages 0 to 11, give 3 pellets) as needed or as directed by a healthcare professional. Under age 2, crush or dissolve pellets in purified water. Sensitive persons begin with 1 pellet and gradually increase to full dose.

OTC - ACTIVE INGREDIENT SECTION

Anthracinum 30x, Influenzinum 30x, Pyrogenium 30x, Bufo rana 15x, Aconitum nap. 10x, Agaricus musc. 10x, Aralia quinquefolia 10x, Baptisia 10x, Bryonia 10x, Chelidonium majus 10x, Eupatorium perf. 10x, Hepar sulph. calc. 10x, Lachesis 10x, Lycopodium 10x, Nux vom. 10x, Rhus toxicodendron 10x, Sanguinaria 10x, Sulphur 10x, Thuja occ. 10x, Echinacea 3x.

OTC - PURPOSE SECTION

Formulated for symptoms associated with colds and infections. Begin at the onset of symptoms.

INACTIVE INGREDIENT SECTION

Inactive Ingredients: Gluten-free, non-GMO, beet-derived sucrose pellets.

QUESTIONS SECTION

www.newtonlabs.net Newton Laboratories, Inc. FDA Est # 1051203 - Conyers, GA 30012
Questions? 1.800.448.7256

WARNINGS SECTION

Warning: Do not use if tamper - evident seal is broken or missing. Consult a licensed healthcare professional if pregnant, nursing or if symptoms worsen or persist for more than a few days. Keep out of reach of children.

OTC - PREGNANCY OR BREAST FEEDING SECTION

Consult a licensed healthcare professional if pregnant, nursing or if symptoms worsen or persist for more than a few days.

OTC - KEEP OUT OF REACH OF CHILDREN SECTION

Keep out of reach of children.